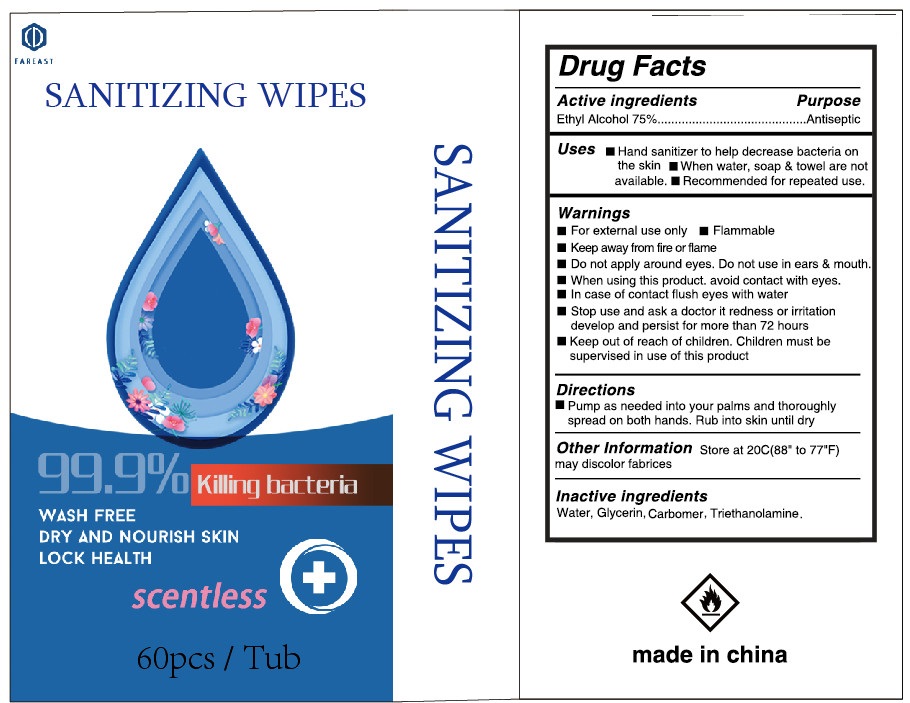 DRUG LABEL: alcohol wipes
NDC: 78623-153 | Form: CLOTH
Manufacturer: ningbo fareast industry co.,ltd
Category: otc | Type: HUMAN OTC DRUG LABEL
Date: 20200826

ACTIVE INGREDIENTS: ALCOHOL 75 mL/100 mL
INACTIVE INGREDIENTS: WATER

60patch in 1 cylinder NDC:78623-153-01

Active ingredient(s)

alcohol 75% v/v purpose :antiseptic

Use

to help reduce bacteria that potentially can cause disease.for use when soap and water are not available

Warnings

for external use only,flammable,keep away from heat or flame

do not use

. in children less than 2 months of age

.on open skin wounds

when using this product keep out of eyes,ears,and mouth in case of contact with eyes,rinse eyes thorough with water

stop use and ask a doctor if irritation or rash occurs,these may be signs of a serious condition.

keep out of reach of children,if swallowed,get medical help or contact a poison control center right away.

stop use and ask a doctor if irriation or rash occurs,these may be signs of a serious condition

keep out of reach of children,if swallowed,get medical help or contact a poison control center right away.

directions

place enough product on hands to cover all surfaces,rub hands together until dry.

supervise children under 6 years of age when using this product to avoid swallowing.

package label principal display panel

25ml in 1 cylinder NDC:78623-153-01